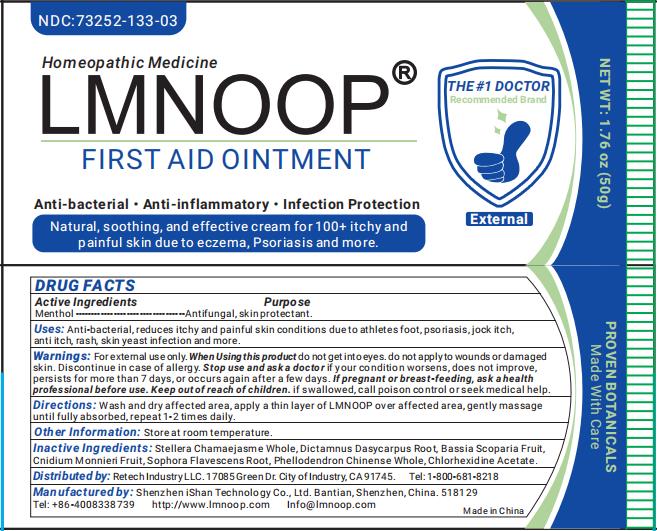 DRUG LABEL: LMNOOP
NDC: 73076-132 | Form: CREAM
Manufacturer: Shenzhen iShan Technology Co., Ltd
Category: homeopathic | Type: HUMAN OTC DRUG LABEL
Date: 20260212

ACTIVE INGREDIENTS: MENTHOL 3 g/100 g
INACTIVE INGREDIENTS: PHELLODENDRON CHINENSE WHOLE 5 g/100 g; BASSIA SCOPARIA FRUIT 3 g/100 g; CNIDIUM MONNIERI FRUIT 3 g/100 g; STELLERA CHAMAEJASME WHOLE 3 g/100 g; DICTAMNUS DASYCARPUS ROOT 3 g/100 g; CHLORHEXIDINE ACETATE 0.351 g/100 g; SOPHORA FLAVESCENS ROOT 5 g/100 g

Active Ingredients

Menthol

Inactive Ingredients

STELLERA CHAMAEJASME WHOLE
DICTAMNUS DASYCARPUS ROOT
BASSIA SCOPARIA FRUIT
CNIDIUM MONNIERI FRUIT
SOPHORA FLAVESCENS ROOT
PHELLODENDRON CHINENSE WHOLE
CHLORHEXIDINE ACETATE

Keep out of reach of children if swallowed, call poison control or seek medical help.

Consulting a doctor before using

If pregnant or breast-feeding, ask a health professional before use.

Stop use and ask a doctor

if your condition worsens, does not improve, persists for more than 7 days, or occurs again after a few days.

Purpose

Anti-inflammatory, help heal.

Other information

Store at room temperature, may stain fabric

Directions

Wash and dry affected area, apply a thin layer of LMNOOP over affected area, Gently
massage until fully absorbed, repeat 1-2 times daily

When using this product

do not get into eyes. do not apply to wounds or damaged skin. discontinue in case of allergy.

Warnings

External use only.